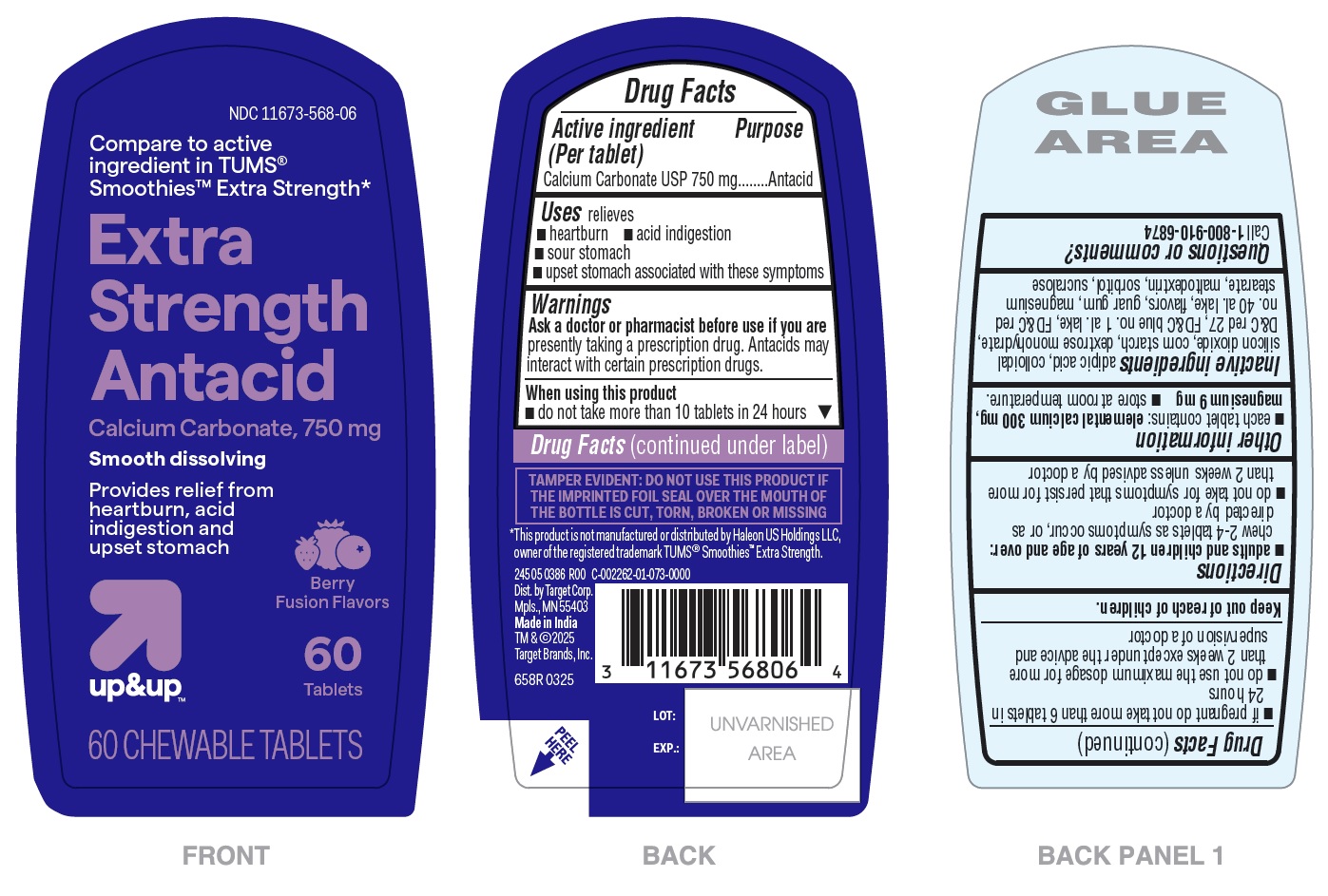 DRUG LABEL: Extra Strength Antacid Smooth dissolving - Berry Fusion Flavors
NDC: 11673-568 | Form: TABLET, CHEWABLE
Manufacturer: TARGET CORPORATION
Category: otc | Type: HUMAN OTC DRUG LABEL
Date: 20250405

ACTIVE INGREDIENTS: CALCIUM CARBONATE 750 mg/1 1
INACTIVE INGREDIENTS: FD&C BLUE NO. 1 ALUMINUM LAKE; GUAR GUM; MAGNESIUM STEARATE; ADIPIC ACID; STARCH, CORN; D&C RED NO. 27; FD&C RED NO. 40 ALUMINUM LAKE; MALTODEXTRIN; SORBITOL; SUCRALOSE; SILICON DIOXIDE; DEXTROSE MONOHYDRATE

658R Target-Calcium Carbonate 750mg Smooth Dissolving Chewable Tablets – Berry Fusion

Drug Facts

Active ingredient (Per tablet)

Calcium Carbonate USP 750 mg

Purpose

Antacid

INDICATIONS AND USAGE

Uses relieves

- heartburn
- acid indigestion
- sour stomach
- upset stomach associated with these symptoms

Warnings

Ask a doctor or pharmacist before use if you are presently taking a prescription drug. Antacids may interact with certain prescription drugs.

When using this product

- do not take more than 10 tablets in 24 hours
- if pregnant do not take more than 6 tablets in 24 hours
- do not use the maximum dosage for more than 2 weeks except under the advice and supervision of a doctor

Keep out of reach of children.

Directions

- adults and children 12 years of age and over: chew 2 – 4 tablets as symptoms occur, or as directed by a doctor
- do not take for symptoms that persist for more than 2 weeks unless advised by a doctor

Other information

- each tablet contains : elemental calcium 300 mg, magnesium 9 mg
- store at room temperature.

INACTIVE INGREDIENT

Inactive ingredients adipic acid, colloidal silicon dioxide, corn starch, dextrose monohydrate, D&C red 27, FD&C blue no. 1 al. lake, FD&C red 40 al. lake, flavors, guar gum, magnesium stearate, maltodextrin, sorbitol, sucralose

Questions or comments? Call 1-800-910-6874